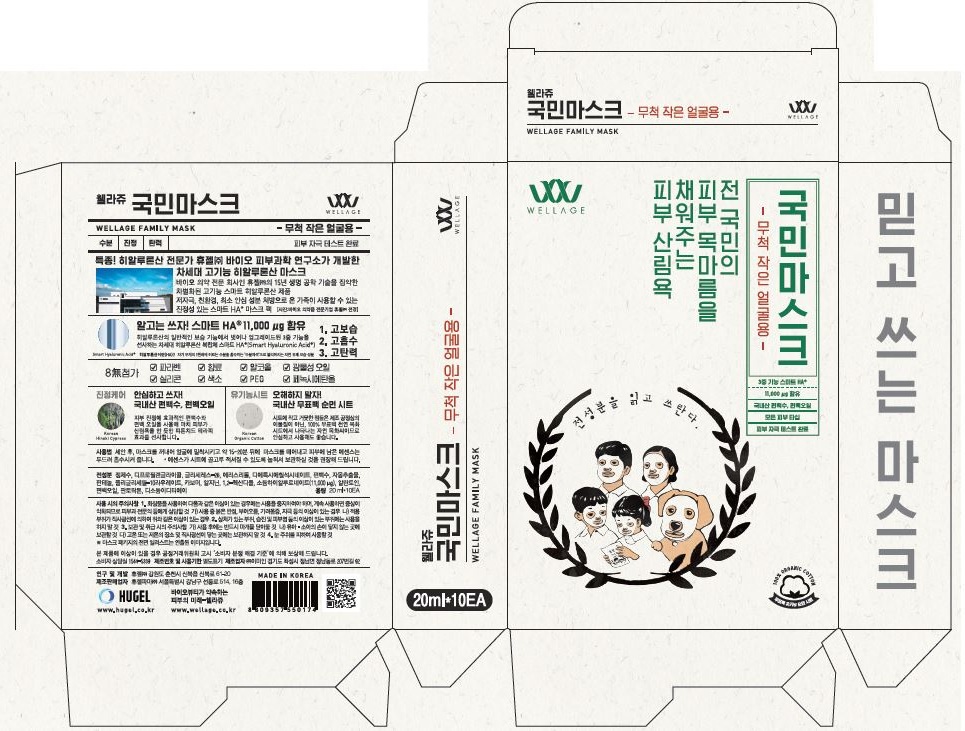 DRUG LABEL: WELLAGE FAMILY MASK SMALL
NDC: 69346-0001 | Form: PATCH
Manufacturer: HUGEL PHARMA CO.,LTD
Category: otc | Type: HUMAN OTC DRUG LABEL
Date: 20160912

ACTIVE INGREDIENTS: HYALURONATE SODIUM 0.056 g/100 mL
INACTIVE INGREDIENTS: WATER; ERYTHRITOL; ALLANTOIN; CHAMAECYPARIS OBTUSA WOOD OIL

Drug Facts

ACTIVE INGREDIENT

Sodium Hyaluronate

INACTIVE INGREDIENT

Water, Dipropylene Glycol, Glycereth-26, Erythritol, Diethoxyethyl Succinate, Chamaecyparis Obtusa Water, Panthenol, Polyglyceryl-10 Laurate, Carbomer, Arginine, 1,2-Hexanediol, Allantoin, Chamaecyparis Obtusa Oil, Pantolactone, Disodium EDTA

PURPOSE

Skin protectant

keep out of reach of the children

INDICATIONS AND USAGE

1. Remove mask from pouch and place on face for 15-20 minutes.
2. Pat in remaining essence to absorb into skin.
  *Masks should be stored lying flat to ensure essence is evenly distributed throughout the sheets.

WARNINGS

1. Do not use in the following cases(Eczema and scalp wounds)

2.Side Effects

1)Due to the use of this product, if rash, irritation, itching and symptopms of hypersnesitivity occur dicontinue use and consult your pharmacist or doctor

3.General Precautions

1)If in contact with the eyes, wash out thoroughty with water If the symptoms are servere, seek medical advice immediately

2)This product is for exeternal use only. Do not use for internal use

4.Storage and handling precautions

1)If possible, avoid direct sunlight and store in cool and area of low humidity

2)In order to maintain the quality of the product and avoid misuse

3)Avoid placing the product near fire and store out in reach of children

DOSAGE AND ADMINISTRATION

for external use only